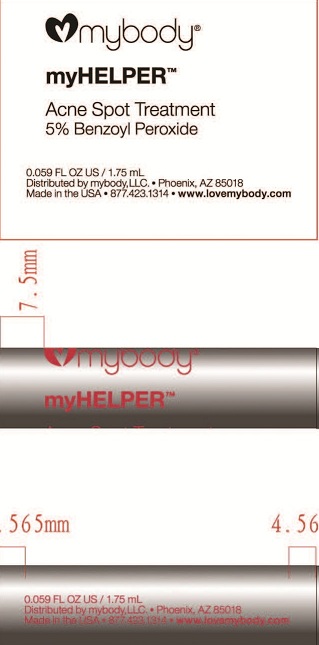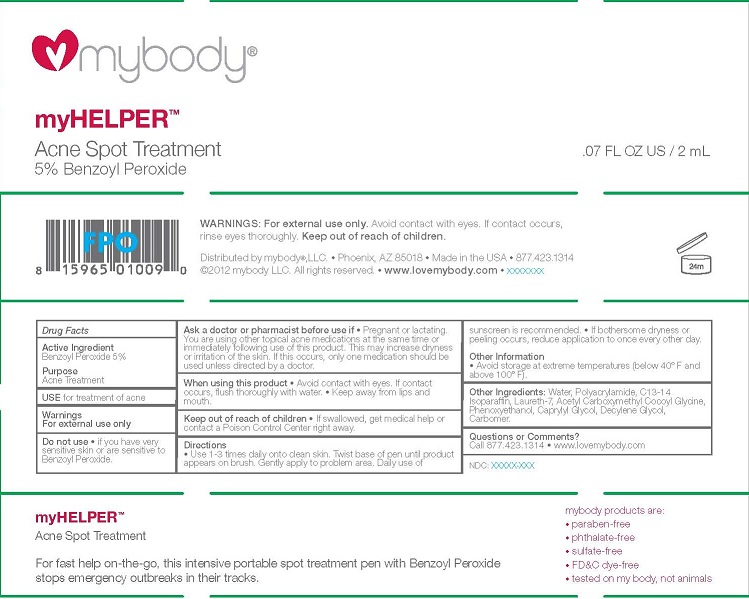 DRUG LABEL: myHELPER
NDC: 49520-102 | Form: CREAM
Manufacturer: mybody
Category: otc | Type: HUMAN OTC DRUG LABEL
Date: 20120503

ACTIVE INGREDIENTS: BENZOYL PEROXIDE 5 g/100 mL
INACTIVE INGREDIENTS: WATER; POLYACRYLAMIDE (1500 MW); C13-14 ISOPARAFFIN; LAURETH-7; ACETYL CARBOXYMETHYL COCOYL GLYCINE; PHENOXYETHANOL; CAPRYLYL GLYCOL; DECYLENE GLYCOL; CARBOMER HOMOPOLYMER (ALLYL SUCROSE CROSSLINKED)

myHELPER

ACTIVE INGREDIENT

BENZOYL PEROXIDE 5%

PURPOSE

ACNE TREATMENT

INDICATIONS AND USAGE

USE FOR TREATMENT OF ACNE

WARNINGS
FOR EXTERNAL USE ONLY

DO NOT USE

- IF YOU HAVE VERY SENSITIVE SKIN OR ARE SENSITIVE TO BENZOYL PEROXIDE.

ASK A DOCTOR OR PHARMACIST BEFORE USE IF

- PREGNANT OR LACTATING. YOU ARE USING OTHER TOPICAL ACNE MEDICATIONS AT THE SAME TIME OR IMMEDIATELY FOLLOWING USE OF THIS PRODUCT. THIS MAY INCREASE DRYNESS OR IRRITATION OF THE SKIN. IF THIS OCCURS, ONLY ONE MEDICATION SHOULD BE USED UNLESS DIRECTED BY A DOCTOR.

WHEN USING THIS PRODUCT

- AVOID CONTACT WITH EYES. IF CONTACT OCCURS, FLUSH THOROUGHLY WITH WATER.
- KEEP AWAY FROM LIPS AND MOUTH.

KEEP OUT OF REACH OF CHILDREN

- IF SWALLOWED, GET MEDICAL HELP OR CONTACT A POISON CONTROL CENTER RIGHT AWAY.

DIRECTIONS

- USE 1-3 TIMES DAILY ONTO CLEAN SKIN. TWIST BASE OF PEN UNTIL PRODUCT APPEARS ON BRUSH. GENTLY APPLY TO PROBLEM AREA. DAILY USE OF SUNSCREEN IS RECOMMENDED.
- IF BOTHERSOME DRYNESS OR PEELING OCCURS, REDUCE APPLICATION TO ONCE EVERY OTHER DAY.

OTHER INFORMATION

- AVOID STORAGE AT EXTREME TEMPERATURES (BELOW 40°F AND ABOVE 100°F).

INACTIVE INGREDIENT

OTHER INGREDIENTS: WATER, POLYACRYLAMIDE, C13-14 ISOPARAFFIN, LAURETH-7, ACETYL CARBOXYMETHYL COCOYL GLYCINE, PHENOXYETHANOL, CAPRYLYL GLYCOL, DECYLENE GLYCOL, CARBOMER.

QUESTIONS OR COMMENTS?

CALL 877.423.1314

- WWW.LOVEMYBODY.COM

PACKAGE LABEL

MYBODY

MYHELPER

ACNE SPOT TREATMENT
5% BENZOYL PEROXIDE
.07 FL OZ US / 2 ML